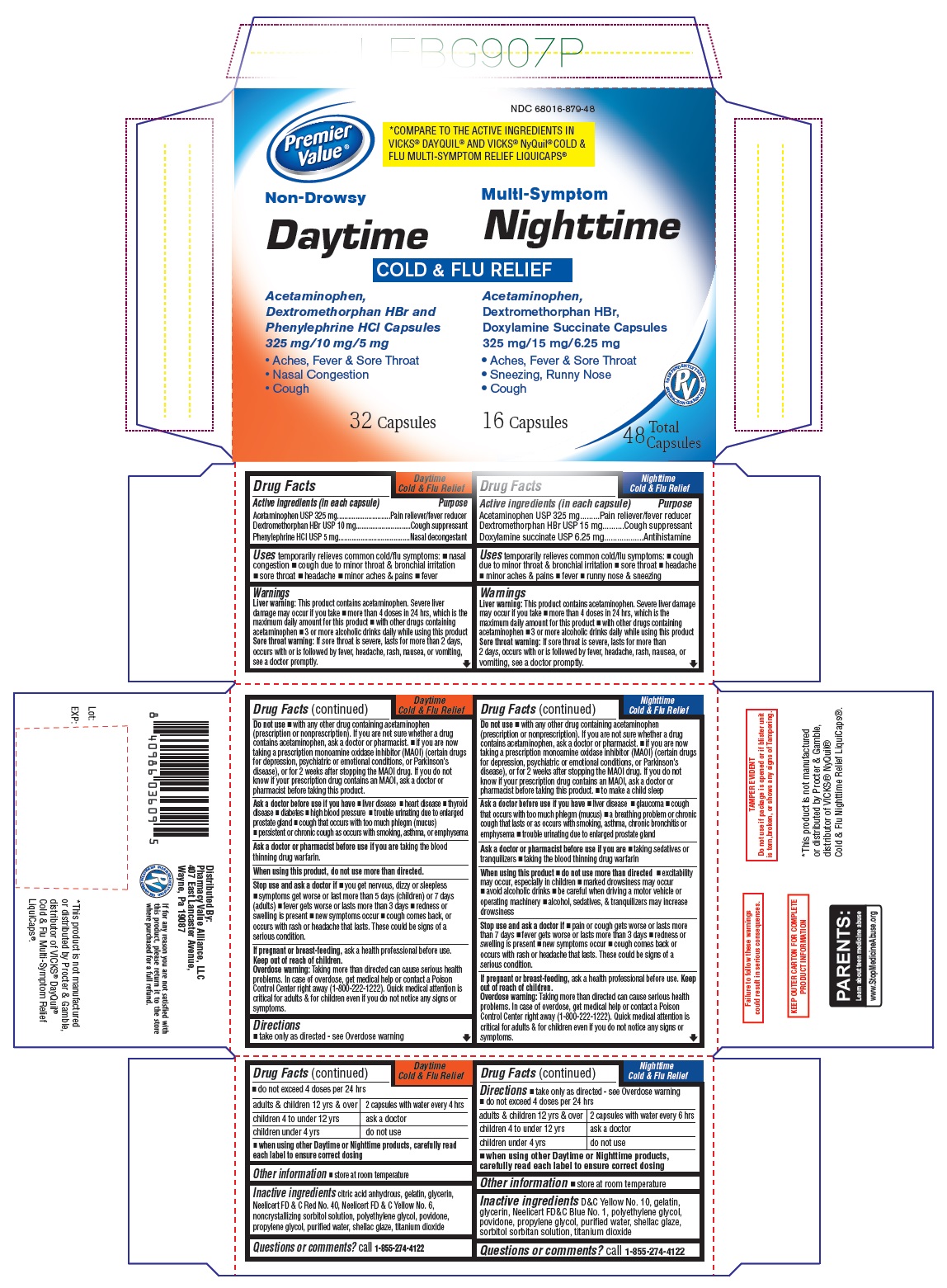 DRUG LABEL: COLD AND FLU MULTI-SYMPTOM RELIEF/COLD AND FLU NIGHTTIME RELIEF
NDC: 68016-879 | Form: KIT | Route: ORAL
Manufacturer: Chain Drug Consortium, LLC
Category: otc | Type: Human OTC Drug Label
Date: 20241024

ACTIVE INGREDIENTS: ACETAMINOPHEN 325 mg/1 1; DEXTROMETHORPHAN HYDROBROMIDE 10 mg/1 1; PHENYLEPHRINE HYDROCHLORIDE 5 mg/1 1; ACETAMINOPHEN 325 mg/1 1; DEXTROMETHORPHAN HYDROBROMIDE 15 mg/1 1; DOXYLAMINE SUCCINATE 6.25 mg/1 1
INACTIVE INGREDIENTS: ANHYDROUS CITRIC ACID; GELATIN, UNSPECIFIED; GLYCERIN; FD&C RED NO. 40; FD&C YELLOW NO. 6; SORBITOL; POLYETHYLENE GLYCOL, UNSPECIFIED; POVIDONE, UNSPECIFIED; PROPYLENE GLYCOL; WATER; SHELLAC; TITANIUM DIOXIDE; D&C YELLOW NO. 10; GELATIN, UNSPECIFIED; GLYCERIN; FD&C BLUE NO. 1; POLYETHYLENE GLYCOL, UNSPECIFIED; POVIDONE, UNSPECIFIED; PROPYLENE GLYCOL; WATER; SHELLAC; SORBITOL; TITANIUM DIOXIDE

Drug Facts - Day Time

Active ingredients (in each capsule)
Acetaminophen USP 325 mg
Dextromethorphan HBr USP 10 mg
Phenylephrine HCl USP 5 mg

Drug Facts - Night Time

Active ingredients (in each capsule)
Acetaminophen USP 325 mg
Dextromethorphan HBr USP 15 mg
Doxylamine succinate USP 6.25 mg

Purpose - Day Time

Pain reliever/fever reducer
Cough suppressant
Nasal decongestant

Purpose - Night Time

Pain reliever/fever reducer
Cough suppressant
Antihistamine

Uses - Day Time

temporarily relieves common cold/flu symptoms:

-
  - nasal congestion
  - cough due to minor throat & bronchial irritation
  - sore throat
  - headache
  - minor aches & pains
  - fever

Uses - Night Time

temporarily relieves common cold/flu symptoms:

-
  - nasal congestion
  - cough due to minor throat & bronchial irritation
  - sore throat
  - headache
  - minor aches & pains
  - fever
  - runny nose & sneezing

Warnings - Day Time

Liver warning: This product contains acetaminophen. Severe liver damage may occur if you take

- more than 4 doses in 24 hrs, which is the maximum daily amount for this product
- with other drugs containing acetaminophen
- 3 or more alcoholic drinks daily while using this product

Sore throat warning: If sore throat is severe, lasts for more than 2 days, occurs with or is followed by fever, headache, rash, nausea, or vomiting, see a doctor promptly.

Warnings - Night Time

Liver warning: This product contains acetaminophen. Severe liver damage may occur if you take

- more than 4 doses in 24 hrs, which is the maximum daily amount for this product
- with other drugs containing acetaminophen
- 3 or more alcoholic drinks daily while using this product

Sore throat warning: If sore throat is severe, lasts for more than 2 days, occurs with or is followed by fever, headache, rash, nausea, or vomiting, see a doctor promptly.

Do not use - Day Time

- with any other drug containing acetaminophen (prescription or nonprescription). If you are not sure whether a drug contains acetaminophen, ask a doctor or pharmacist.
- if you are now taking a prescription monoamine oxidase inhibitor (MAOI) (certain drugs for depression, psychiatric or emotional conditions, or Parkinson's disease), or for 2 weeks after stopping the MAOI drug. If you do not know if your prescription drug contains an MAOI, ask a doctor or pharmacist before taking this product.

Do not use - Night Time

- with any other drug containing acetaminophen (prescription or nonprescription). If you are not sure whether a drug contains acetaminophen, ask a doctor or pharmacist.
- If you are now taking a prescription monoamine oxidase inhibitor (MAOI) (certain drugs for depression, psychiatric or emotional conditions, or Parkinson's disease), or for 2 weeks after stopping the MAOI drug. If you do not know if your prescription drug contains an MAOI, ask a doctor or pharmacist before taking this product.
- to make a child sleep

Ask a doctor before use if you have - Day Time

- liver disease
- heart disease
- thyroid disease
- diabetes
- high blood pressure
- trouble urinating due to enlarged prostate gland
- cough that occurs with too much phlegm (mucus)
- persistent or chronic cough as occurs with smoking, asthma, or emphysema

Ask a doctor before use if you have - Night Time

- liver disease
- glaucoma
- cough that occurs with too much phlegm (mucus)
- a breathing problem or chronic cough that lasts or as occurs with smoking, asthma, chronic bronchitis or emphysema
- trouble urinating due to enlarged prostate gland

Ask a doctor or pharmacist before use if you are - Day Time

taking the blood thinning drug warfarin

Ask a doctor or pharmacist before use if you are - Night Time

- taking sedatives or tranquilizers
- taking the blood thinning drug warfarin

When using this product,

do not use more than directed.

When using this product - Night Time

- do not use more than directed
- excitability may occur, especially in children
- marked drowsiness may occur
- avoid alcoholic drinks
- be careful when driving a motor vehicle or operating machinery
- alcohol, sedatives, & tranquilizers may increase drowsiness

Stop use and ask a doctor if - Day Time

- you get nervous, dizzy or sleepless
- symptoms get worse or last more than 5 days (children) or 7 days (adults)
- fever gets worse or lasts more than 3 days
- redness or swelling is present
- new symptoms occur
- cough comes back, or occurs with rash or headache that lasts.

These could be signs of a serious condition.

Stop use and ask a doctor if - Night Time

- pain or cough gets worse or lasts more than 7 days
- fever gets worse or lasts more than 3 days
- redness or swelling is present
- new symptoms occur
- cough comes back or occurs with rash or headache that lasts.

These could be signs of a serious condition.

If pregnant or breast-feeding,

ask a health professional before use.

If pregnant or breast-feeding, - Night Time

ask a health professional before use.

Keep out of reach of children. - Day Time

Overdose warning:
Taking more than directed can cause serious health problems. In case of overdose, get medical help or contact a Poison Control Center right away (1-800-222-1222). Quick medical attention is critical for adults & for children even if you do not notice any signs or symptoms.

Keep out of reach of children. - Night Time

Overdose warning:
Taking more than directed can cause serious health problems. In case of overdose, get medical help or contact a Poison Control Center right away (1-800-222-1222). Quick medical attention is critical for adults & for children even if you do not notice any signs or symptoms.

Directions - Day Time

- take only as directed – see Overdose warning
- do not exceed 4 doses per 24 hours

adults & children 12 yrs & over | 2 capsules with water every 4 hrs
children 4 to under 12 yrs | ask a doctor
children under 4 yrs | do not use

when using other Daytime or Nighttime products, carefully read each label to ensure correct dosing

Directions - Night Time

- take only as directed – see Overdose warning
- do not exceed 4 doses per 24 hours

adults & children 12 yrs & over | 2 capsules with water every 6 hrs
children 4 to under 12 yrs | ask a doctor
children under 4 yrs | do not use

when using other Daytime or Nighttime products, carefully read each label to ensure correct dosing

Other information - Day Time

- store at room temperature

Other information - Night Time

- store at room temperature

Inactive ingredients - Day Time

citric acid anhydrous, gelatin, glycerin, Neelicert FD & C Red No. 40, Neelicert FD & C Yellow No. 6, noncrystallizing sorbitol solution, polyethylene glycol, povidone, propylene glycol, purified water, shellac glaze, titanium dioxide

Inactive ingredients - Night Time

D&C Yellow No. 10, gelatin, glycerin, Neelicert FD&C Blue No. 1, polyethylene glycol, povidone, propylene glycol, purified water, shellac glaze, sorbitol sorbitan solution, titanium dioxide

Questions or comments?

call 1-855-274-4122
Distributed by:
Pharmacy Value Alliance, LLC

407 East Lancaster Avenue,

Wayne, Pa 19087

PACKAGE LABEL-PRINCIPAL DISPLAY PANEL 16 FL OZ (474 mL Bottle)

NDC 68016-879-18
Premier Value®

COMPARE TO THE ACTIVE INGREDIENTS IN
VICKS® DAYQUIL® AND VICKS® Nyquil® COLD &
FLU MULTI-SYMPTOM RELIEF LIQUICAPS®

Non-Drowsy Multi-Symptom
Daytime Nighttime
COLD & FLU RELIEF
Acetaminophen, Acetaminophen,
Dextromethorphan HBr and Dextromethorphan HBr,
Phenylephrine HCl Capsules Doxylamine Succinate Capsules
325 mg/10 mg/5 mg 325 mg/15 mg/6.25 mg
• Aches, Fever & Sore Throat • Aches, Fever & Sore Throat
• Nasal Congestion • Sneezing, Runny Nose
• Cough • Cough
32 Capsules 16 Capsules